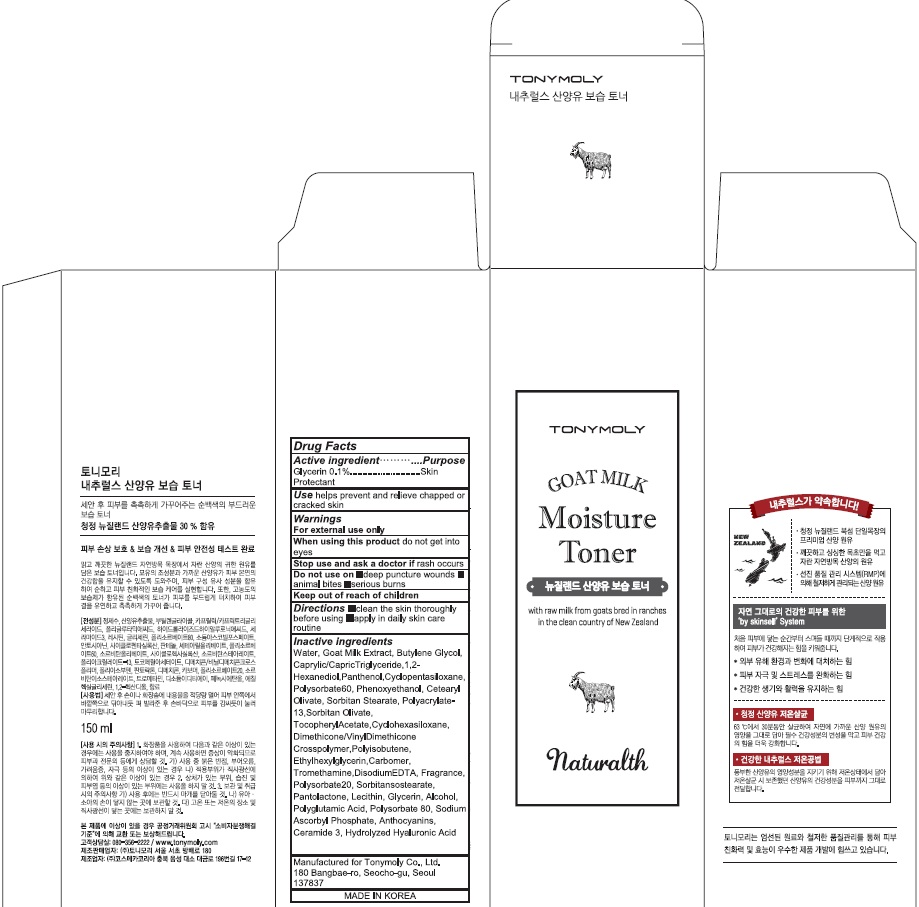 DRUG LABEL: NATURALTH GOAT MILK MOISTURE TONER
NDC: 59078-300 | Form: LIQUID
Manufacturer: TONYMOLY CO.,LTD
Category: otc | Type: HUMAN OTC DRUG LABEL
Date: 20160527

ACTIVE INGREDIENTS: Glycerin 0.15 g/150 mL
INACTIVE INGREDIENTS: Water; Butylene Glycol

ACTIVE INGREDIENT

Active ingredient: Glycerin 0.1%

INACTIVE INGREDIENT

Inactive Ingredient: Water, Goat Milk Extract, Butylene Glycol, Caprylic/CapricTriglyceride,1,2-Hexanediol,Panthenol,Cyclopentasiloxane,Polysorbate60, Phenoxyethanol, Cetearyl Olivate, Sorbitan Stearate, Polyacrylate-13,Sorbitan Olivate, TocopherylAcetate,Cyclohexasiloxane, Dimethicone/VinylDimethicone Crosspolymer,Polyisobutene, Ethylhexylglycerin,Carbomer, Tromethamine,DisodiumEDTA, Fragrance, Polysorbate20, Sorbitansostearate, Pantolactone, Lecithin, Glycerin, Alcohol, Polyglutamic Acid, Polysorbate 80, Sodium Ascorbyl Phosphate, Anthocyanins, Ceramide 3, Hydrolyzed Hyaluronic Acid

PURPOSE

Purpose: Skin Protectant

WARNINGS

Warnings: For external use only. When using this product do not get into eyes. Stop use and ask a doctor if rash occurs. Do not use on - deep puncture wounds - animal bites - serious burns Keep out of reach of children.

KEEP OUT OF REACH OF CHILDREN

Use

Use: helps prevent and relieve chapped or cracked skin

Directions

Directions: - clean the skin thoroughly before using - apply in daily skin care routine